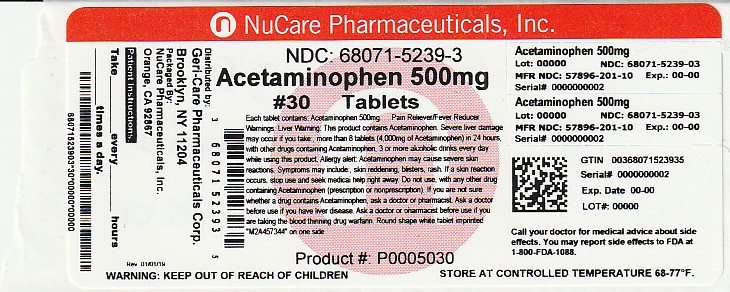 DRUG LABEL: Acetaminophen
NDC: 68071-5239 | Form: TABLET
Manufacturer: NuCare Pharmaceuticals,Inc.
Category: otc | Type: HUMAN OTC DRUG LABEL
Date: 20241231

ACTIVE INGREDIENTS: ACETAMINOPHEN 500 mg/1 1
INACTIVE INGREDIENTS: POVIDONE; SODIUM STARCH GLYCOLATE TYPE A POTATO; STEARIC ACID; CROSPOVIDONE; METHYLPARABEN; PROPYLPARABEN; STARCH, PREGELATINIZED CORN

gc201

Active Ingredients

Acetaminophen 500 mg

Purpose

Pain Reliever/Fever Reducer

Uses

- temporarily relieves minor aches and pains
- temporarily reduces fever

Warnings

Liver warning:

This product contains acetaminophen. Severe liver damage may occur if you take

- more than 8 tablets in 24 hours, which is the maximum daily amount
- with other drugs containing acetaminophen
- 3 or more alcoholic drinks every day while using this product

Do not use

- with any other drug containing acetaminophen (prescription or nonprescription). If you are not sure whether a drug contains acetaminophen, ask a doctor or pharmacist.

Ask a doctor before use if you have

liver disease.

Ask a doctor or pharmacist before use if you are

taking the blood thinning drug warfarin.

Stop use and ask a doctor if

- pain gets worse or lasts more than 10 days
- fever gets worse or lasts more than 3 days
- new symptom occur
- redness or swelling is present

These could be signs of a serious condition.

If pregnant or breast-feeding, ask a health professional before use.

Overdose Warning:

Taking more than the recommended dose (overdose) may cause liver damage. In case of overdose, get medical help or contact a Poison Control Center right away. Quick medical attention is critical for adults as well as for children even if you do not notice any signs or symptoms.

Keep out of reach of children.

Directions

- do not take more than directed
- adults and children 12 years and over: take 1-2 tablets every 4-6 hours, as needed; not more than 8 tablets in 24 hours
- children under 12 years: do not use

Other Information

- TAMPER EVIDENT: Do not use if imprinted seal under cap is missing or broken.
- store at 20⁰C-25⁰C (68⁰F-77⁰F)
- for institutional use only

Inactive Ingredients

povidone, sodium starch glycolate, starch, stearic acid. May also contain: crospovidone, methylparaben and propylparaben